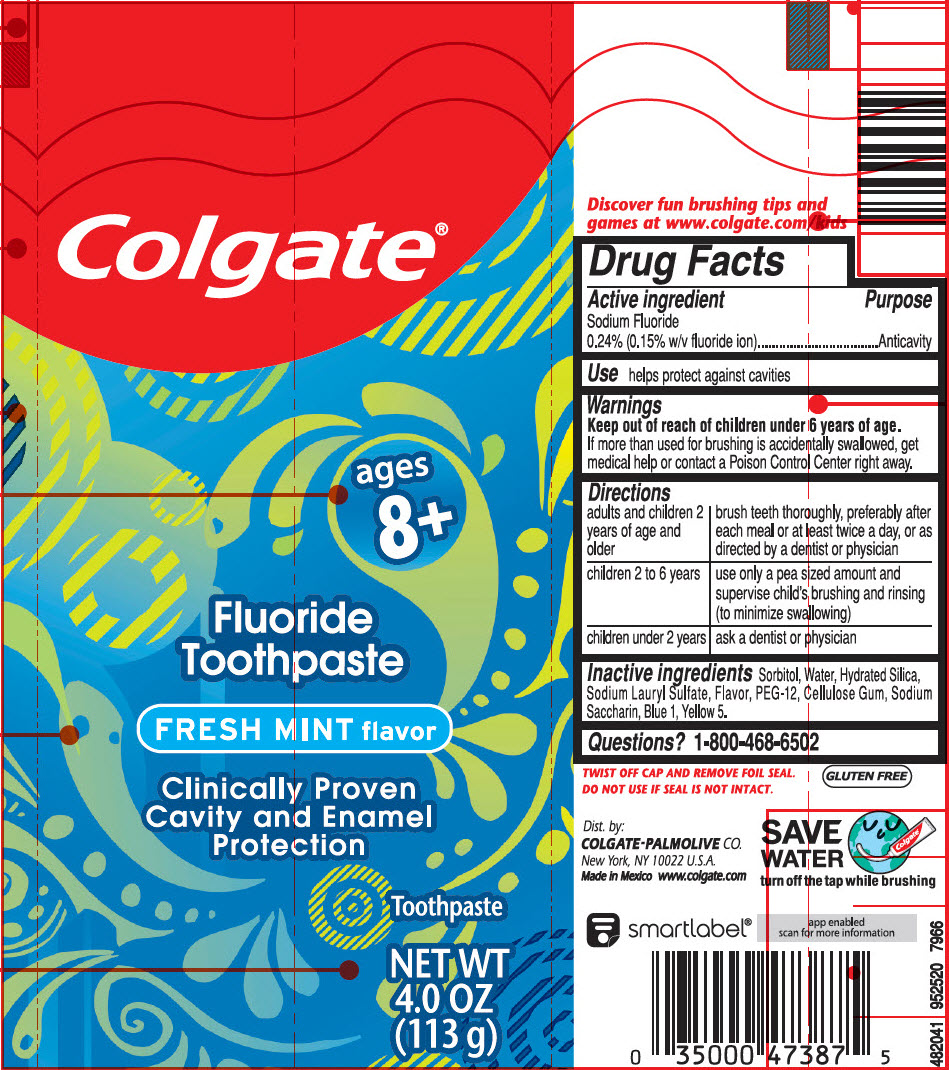 DRUG LABEL: Colgate  Cavity  Protection  Fresh Mint
NDC: 65954-061 | Form: GEL, DENTIFRICE
Manufacturer: Mission Hills S.A de C.V
Category: otc | Type: HUMAN OTC DRUG LABEL
Date: 20190729

ACTIVE INGREDIENTS: SODIUM FLUORIDE 1.1 mg/1 g
INACTIVE INGREDIENTS: SORBITOL 680 mg/1 g; WATER; HYDRATED SILICA; SODIUM LAURYL SULFATE; POLYETHYLENE GLYCOL 600; CARBOXYMETHYLCELLULOSE SODIUM, UNSPECIFIED; SACCHARIN SODIUM; FD&C BLUE NO. 1; FD&C YELLOW NO. 5

Colgate® Cavity Protection Fresh Mint

Drug Facts

Active ingredient

Sodium Fluoride 0.24% (0.15% w/v fluoride ion)

Purpose

Anticavity

Use

helps protect against cavities

Warnings

Keep out of reach of children under 6 years of age.

If more than used for brushing is accidentally swallowed, get medical help or contact a Poison Control Center right away.

Directions

adults and children 2 years of age and older | brush teeth thoroughly, preferably after each meal or at least twice a day, or as directed by a dentist or physician
children 2 to 6 years | use only a pea sized amount and supervise child's brushing and rinsing (to minimize swallowing)
children under 2 years | ask a dentist or physician

Inactive ingredients

Sorbitol, Water, Hydrated Silica, Sodium Lauryl Sulfate, Flavor, PEG-12, Cellulose Gum, Sodium Saccharin, Blue 1, Yellow 5.

Questions?

1-800-468-6502

Dist. by:
COLGATE-PALMOLIVE CO.
New York, NY 10022 U.S.A.

PRINCIPAL DISPLAY PANEL - 113 g Tube Label

Colgate®

ages
8+

Fluoride
Toothpaste

FRESH MINT flavor

Clinically Proven
Cavity and Enamel
Protection

Toothpaste

NET WT
4.0 OZ
(113 g)